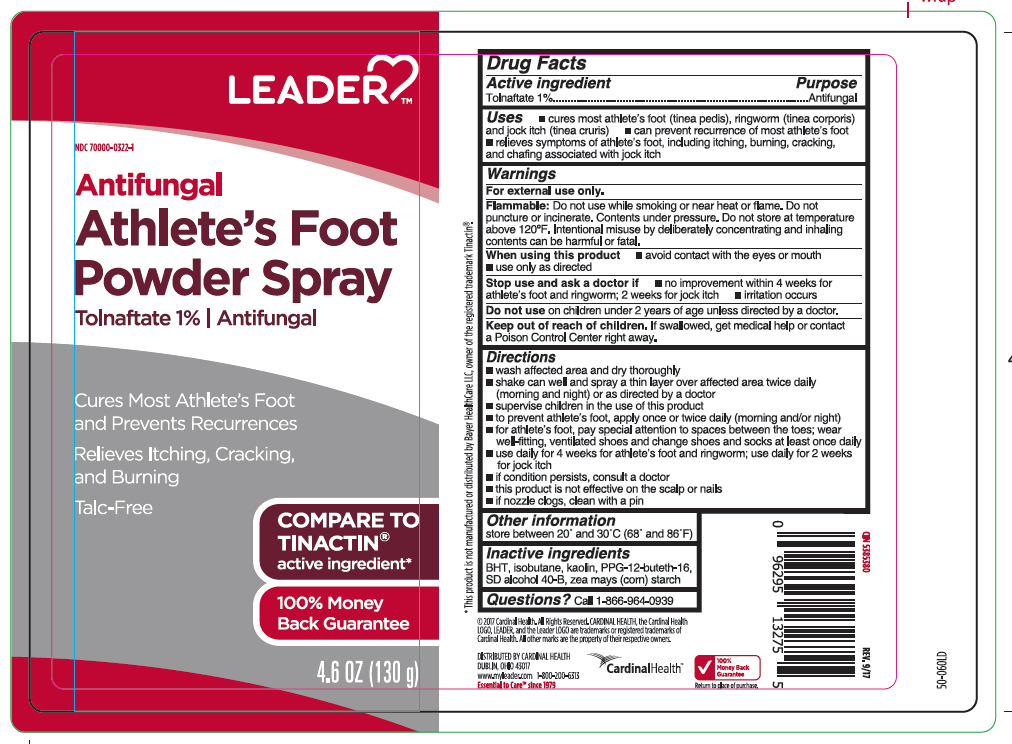 DRUG LABEL: Tolnafate
NDC: 70000-0322 | Form: AEROSOL, SPRAY
Manufacturer: LEADER/ Cardinal Health 110, Inc.
Category: otc | Type: HUMAN OTC DRUG LABEL
Date: 20251231

ACTIVE INGREDIENTS: TOLNAFTATE 1.3 g/130 g
INACTIVE INGREDIENTS: BUTYLATED HYDROXYTOLUENE; ISOBUTANE; KAOLIN; PPG-12-BUTETH-16; ALCOHOL; ZEA MAYS SUBSP. MAYS WHOLE

Leader Tolnaftate Antifungal Powder Spray - Talc-Free

Active ingredient

Tolnaftate 1%

Purpose

Antifungal

Uses

- cures most athlete’s foot (tinea pedis), ringworm (tinea corporis), and jock itch (tinea cruris)
- can prevent recurrence of most athlete’s foot
- relieves symptoms of athlete’s foot, including itching, burning, cracking, and chafing associated with jock itch

WARNINGS

For external use only.

Flammable:

Do not use while smoking or near heat or flame. Do not puncture or incinerate. Contents under pressure. Do not store at temperature above 120ºF. Intentional misuse by deliberately concentrating and inhaling contents can be harmful or fatal.

When using this product

- avoid contact with the eyes or mouth
- use only as directed

Stop use and ask a doctor if

- no improvement within 4 weeks for athlete’s foot and ringworm; 2 weeks for jock itch
- irritation occurs

Do not use

on children under 2 years of age unless directed by a doctor.

Keep out of reach of children.

If swallowed, get medical help or contact a Poison Control Center right away.

Directions

- wash affected area and dry thoroughly
- shake can well and spray a thin layer over affected area twice daily (morning and night) or as directed by a doctor
- supervise children in the use of this product
- for athlete's foot, pay special attention to spaces between the toes; wear well-fitting, ventilated shoes and change shoes and socks at least once daily
- use daily for 4 weeks for athlete’s foot and ringworm; use daily for 2 weeks for jock itch
- if condition persists, consult a doctor
- this product is not effective on the scalp or nails
- if nozzle clogs, clean with a pin

Other information

store between 20º and 30ºC (68ºF and 86º)

Inactive ingredients

BHT, isobutane, kaolin, PPG-12-buteth-16, SD alcohol 40-B, zea mays (corn) starch

Questions?

Call 1-866-964-0939

Principal Display Panel

LEADER

Antifungal

Athlete's Foot

Powder Spray

Tolnaftate 1 % | Antifungal

Cure Most Athlete's Foot

and Prevents Recurrences

Relieves Itching, Cracking,

and Burning

Talc- Free

4.6 OZ (130 g)